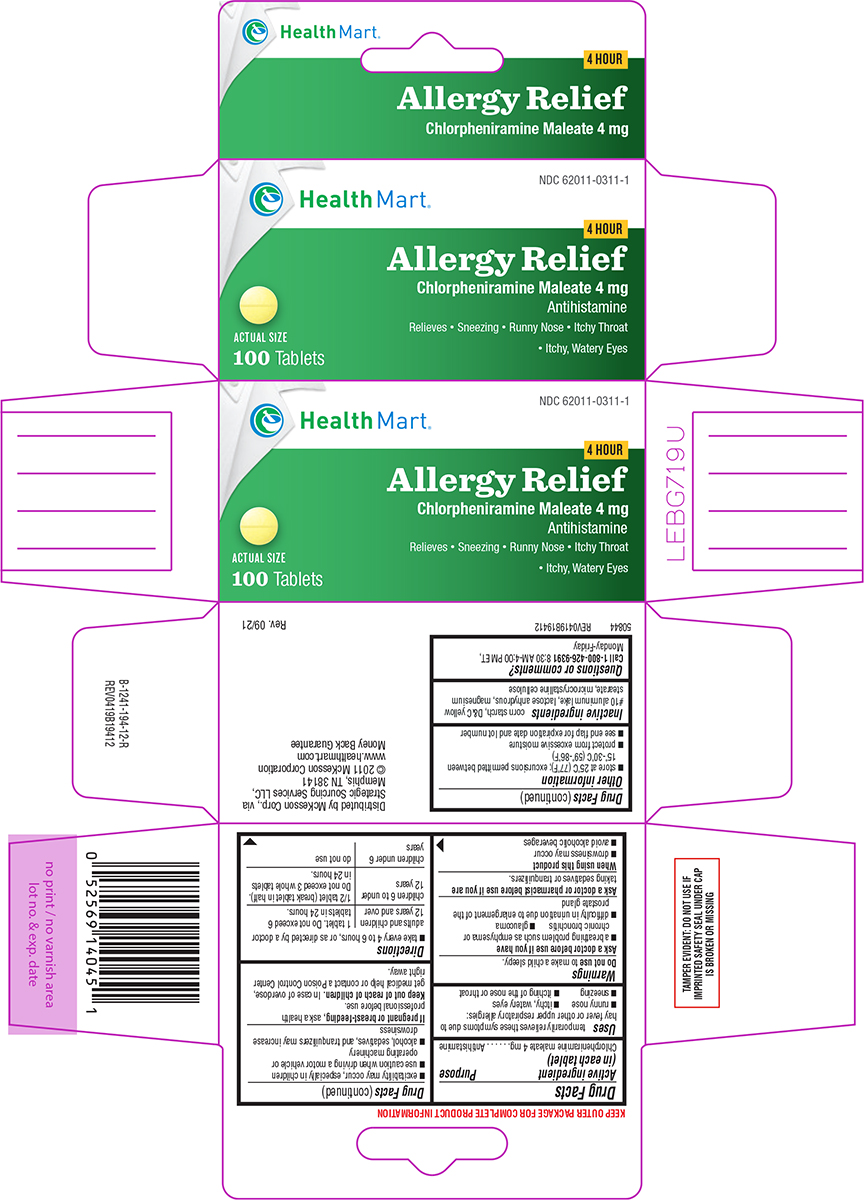 DRUG LABEL: allergy relief
NDC: 62011-0311 | Form: TABLET
Manufacturer: Strategic Sourcing Services, LLC (Health Mart)
Category: otc | Type: HUMAN OTC DRUG LABEL
Date: 20250410

ACTIVE INGREDIENTS: CHLORPHENIRAMINE MALEATE 4 mg/1 1
INACTIVE INGREDIENTS: STARCH, CORN; D&C YELLOW NO. 10 ALUMINUM LAKE; ANHYDROUS LACTOSE; MAGNESIUM STEARATE; MICROCRYSTALLINE CELLULOSE

Health Mart 44-194-Delisted

Active ingredient (in each tablet)

Chlorpheniramine maleate 4 mg

Purpose

Antihistamine

Uses

temporarily relieves these symptoms due to hay fever or other upper respiratory allergies:

- runny nose
- itchy, watery eyes
- sneezing
- itching of the nose or throat

Warnings

Do not use

to make a child sleepy.

Ask a doctor before use if you have

- a breathing problem such as emphysema or chronic bronchitis
- glaucoma
- difficulty in urination due to enlargement of the prostate gland

Ask a doctor or pharmacist before use if you are

taking sedatives or tranquilizers.

When using this product

- drowsiness may occur
- avoid alcoholic beverages
- alcohol, sedatives, and tranquilizers may increase drowsiness
- use caution when driving a motor vehicle or operating machinery
- excitability may occur, especially in children

If pregnant or breast-feeding,

ask a health professional before use.

Keep out of reach of children.

In case of overdose, get medical help or contact a Poison Control Center right away.

Directions

- take every 4 to 6 hours, or as directed by a doctor

adults and children 12 years and over | 1 tablet. Do not exceed 6 tablets in 24 hours.
children 6 to under 12 years | 1/2 tablet (break tablet in half). Do not exceed 3 whole tablets in 24 hours.
children under 6 years | do not use

Other information

- store at 25°C (77°F); excursions permitted between 15°-30°C (59°-86°F)
- protect from excessive moisture
- see end flap for expiration date and lot number

Inactive ingredients

corn starch, D&C yellow #10 aluminum lake, lactose anhydrous, magnesium stearate, microcrystalline cellulose

Questions or comments?

Call 1-800-426-9391 8:30 AM-4:00 PM ET, Monday-Friday

Principal display panel

Health Mart®

NDC 62011-0311-1

4 HOUR

Allergy Relief
Chlorpheniramine Maleate 4 mg
Antihistamine

Relieves • Sneezing • Runny Nose • Itchy Throat
• Itchy, Watery Eyes

Actual Size

100 Tablets

TAMPER EVIDENT: DO NOT USE IF
IMPRINTED SAFETY SEAL UNDER CAP
IS BROKEN OR MISSING

50844 REV0419B19412

Distributed by McKesson Corp., via
Strategic Sourcing Services LLC,
Memphis, TN 38141
© 2011 Mckesson Corporation
www.healthmart.com
Money Back Guarantee

Rev. 09/21

Health Mart B-1241-194-12-R REV0419B